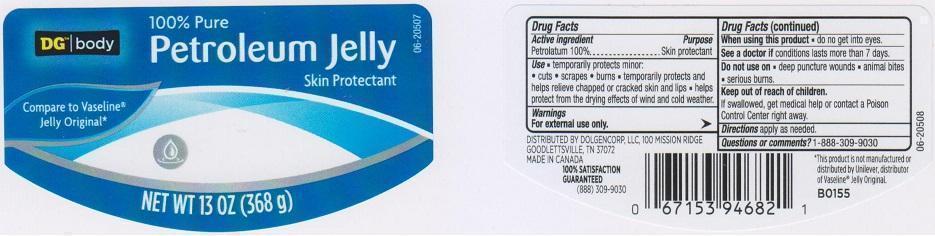 DRUG LABEL: DG BODY
NDC: 55910-350 | Form: JELLY
Manufacturer: DOLGENCORP INC
Category: otc | Type: HUMAN OTC DRUG LABEL
Date: 20150702

ACTIVE INGREDIENTS: PETROLATUM 100 g/100 g

DRUG FACTS

Active Ingredient

Petrolatum 100%

Purpose

Skin protectant

Uses

Temporarily protects minor:

- cuts
- scrapes
- burns
- temporarily protects and helps relieve chapped or cracked skin and lips
- helps protect from the drying effects of wind and cold weather

Warnings

For external use only

When using this product

- do not get into eyes

See a doctor if

conditions lasts more than 7 days

Do not use on

- deep puncture wounds
- animal bites
- serious burns

Keep out of reach of children.

If swallowed, get medical help or contact a poison control center right away.

Directions

apply as needed

Questions or comments?

1-888-309-9030